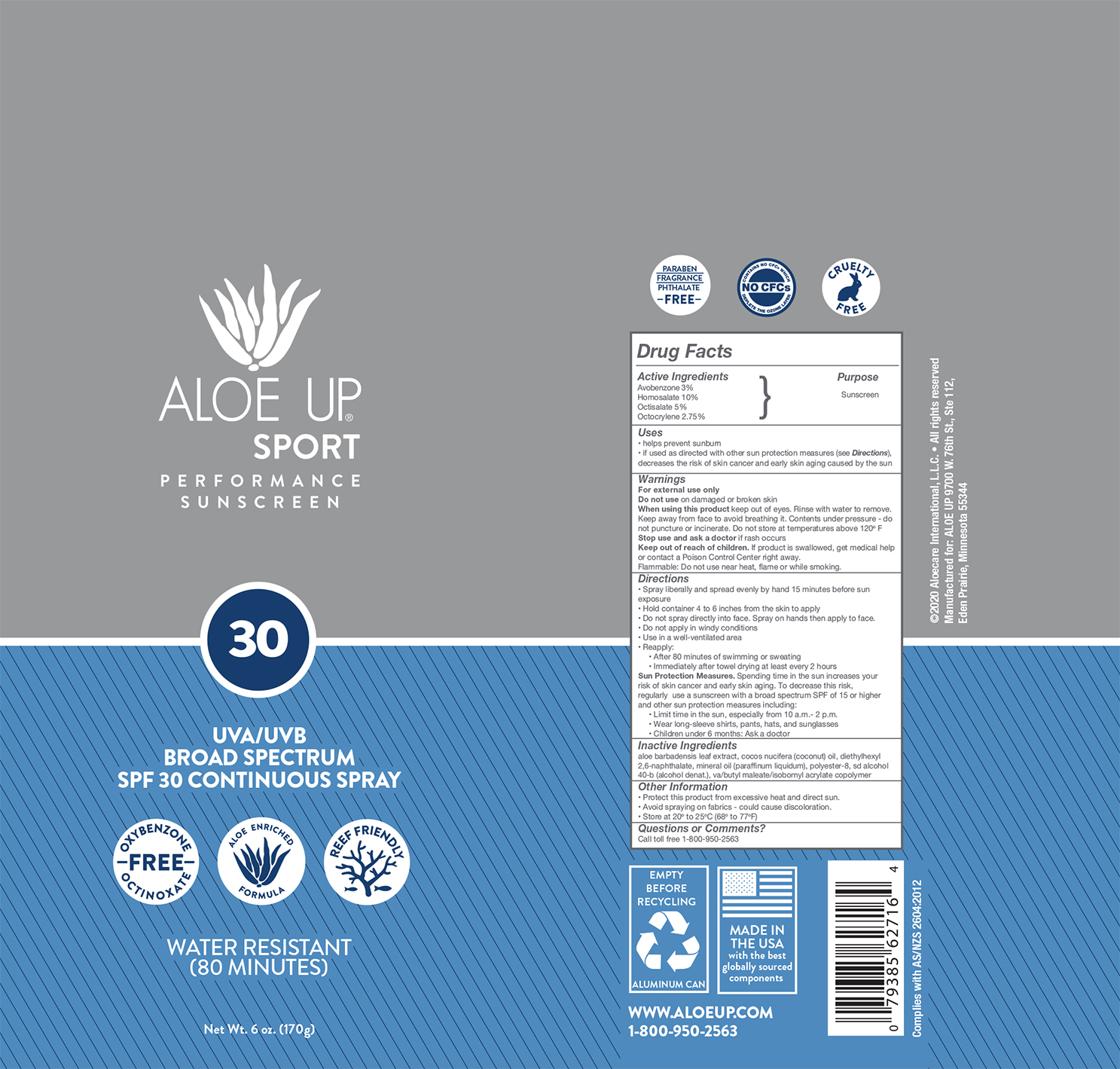 DRUG LABEL: Aloe Up Sport SPF 30 C-Spray
NDC: 73440-2716 | Form: AEROSOL, SPRAY
Manufacturer: Cross Brands Contract Filling
Category: otc | Type: HUMAN OTC DRUG LABEL
Date: 20210219

ACTIVE INGREDIENTS: OCTOCRYLENE 4.7 g/170 g; AVOBENZONE 5.1 g/170 g; HOMOSALATE 17 g/170 g; OCTISALATE 8.5 g/170 g
INACTIVE INGREDIENTS: ALCOHOL 116 g/170 g

Aloe Up Sport SPF 30 C-spray